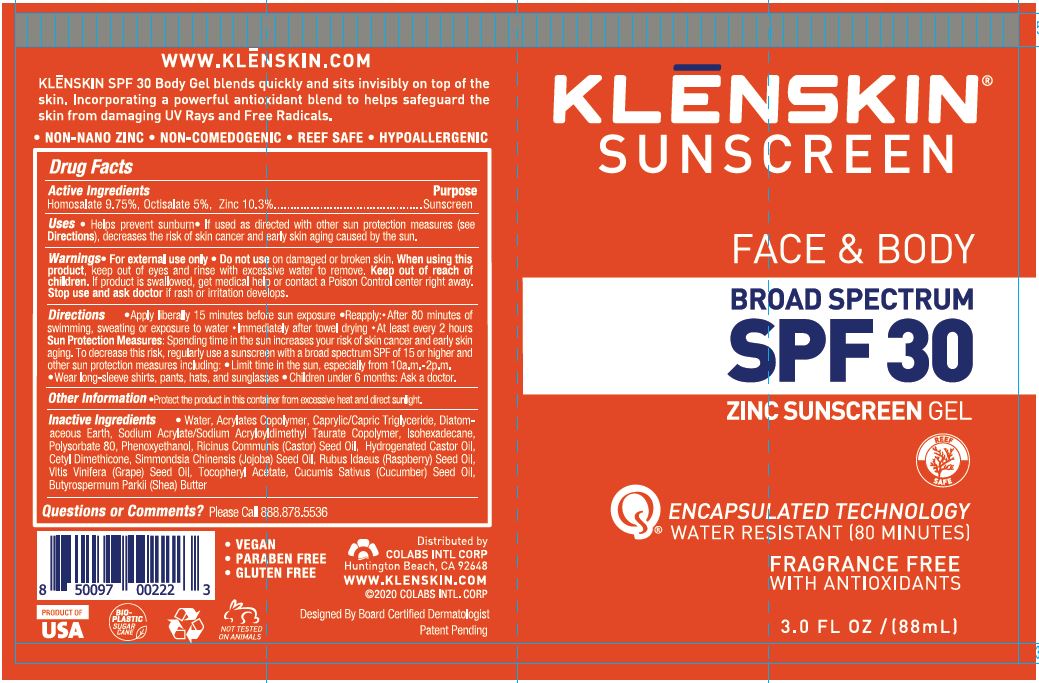 DRUG LABEL: KLENSKIN SUNSCREEN FACE AND BODY BROAD SPECTRUM
NDC: 61369-202 | Form: GEL
Manufacturer: CoLabs Intl. Corp
Category: otc | Type: HUMAN OTC DRUG LABEL
Date: 20240115

ACTIVE INGREDIENTS: HOMOSALATE 9.75 g/100 mL; OCTISALATE 5 g/100 mL; ZINC OXIDE 5 g/100 mL
INACTIVE INGREDIENTS: .ALPHA.-TOCOPHEROL ACETATE; CUCUMBER SEED OIL; SHEA BUTTER; WATER; CARBOMER COPOLYMER TYPE A; MEDIUM-CHAIN TRIGLYCERIDES; DIATOMACEOUS EARTH; SODIUM ACRYLATE/SODIUM ACRYLOYLDIMETHYLTAURATE COPOLYMER (4000000 MW); ISOHEXADECANE; POLYSORBATE 80; PHENOXYETHANOL; CASTOR OIL; HYDROGENATED CASTOR OIL; CETYL DIMETHICONE 45; JOJOBA OIL; RASPBERRY SEED OIL; GRAPE SEED OIL

COLABS - KLENSKIN SUNSCREEN - FACE & BODY SPF 30 SUNSCREEN GEL (61369-202)

ACTIVE INGREDIENTS

HOMOSALATE 9.75%

OCTISALATE 5%

ZINC 10.3%

PURPOSE

SUNSCREEN

USES

- HELPS PREVENT SUNBURN
- IF USED AS DIRECTED WITH OTHER SUN PROTECTION MEASURES (SEE DIRECTIONS), DECREASES THE RISK OF SKIN CANCER AND EARLY SKIN AGING CAUSED BY THE SUN.

WARNINGS

- FOR EXTERNAL USE ONLY
- DO NOT USE ON DAMAGED OR BROKEN SKIN.
- WHEN USING THIS PRODUCT, KEEP OUT OF EYES AND RINSE WITH EXCESSIVE WATER TO REMOVE.

KEEP OUT OF REACH OF CHILDREN. IF PRODUCT IS SWALLOWED, GET MEDICAL HELP OR CONTACT A POISON CONTROL CENTER RIGHT AWAY.

STOP USE AND ASK A DOCTOR IF RASH OR IRRITATION DEVELOPS.

DIRECTIONS

- APPLY LIBERALLY 15 MINUTES BEFORE SUN EXPOSURE
- REAPPLY:
- AFTER 80 MINUTES OF SWIMMING, SWEATING OR EXPOSURE TO WATER
- IMMEDIATELY AFTER TOWEL DRYING
- AT LEAST EVERY 2 HOURS

OTHER SAFETY INFORMATION

SUN PROTECTION MEASURES: SPENDING TIME IN THE SUN INCREASES YOUR RISK OF SKIN CANCER AND EARLY SKIN AGING. TO DECREASE THIS RISK, REGULARLY USE A SUNSCREEN WITH A BROAD SPECTRUM SPF OF 15 OR HIGHER AND OTHER SUN PROTECTION MEASURES INCLUDING:

- LIMIT TIME IN THE SUN, ESPECIALLY FROM 10 A.M. - 2 P.M.
- WEAR LONG-SLEEVED SHIRTS, PANTS, HATS, AND SUNGLASSES
- CHILDREN UNDER 6 MONTHS: ASK A DOCTOR.

OTHER INFORMATION

PROTECT THE PRODUCT IN THIS CONTAINER FROM EXCESSIVE HEAT AND DIRECT SUNLIGHT.

INACTIVE INGREDIENTS

Water, Acrylates Copolymer, Caprylic/Capric Triglyceride, Diatomaceous Earth, Sodium Acrylate/Sodium Acryloyldimethyl Taurate Copolymer, Isohexadecane, Polysorbate 80, Phenoxyethanol, Ricinus Comminus (Castor) Seed Oil, Hydrogenated Castor Oil, Cetyl Dimethicone, Simmondsia Chinensis (Jojoba) Seed Oil, Rubeus Idaeus (Red Raspberry) Oil, Vitus Vinifera (Grape) Seed Oil, Tocopheryl Acetate, Cucumis Sativua (Cucumber) Seed Oil, Butyrospermum Parkii (Shea) Oil

QUESTIONS OR COMMENTS?

PLEASE CALL TOLL FREE 888.878.5536